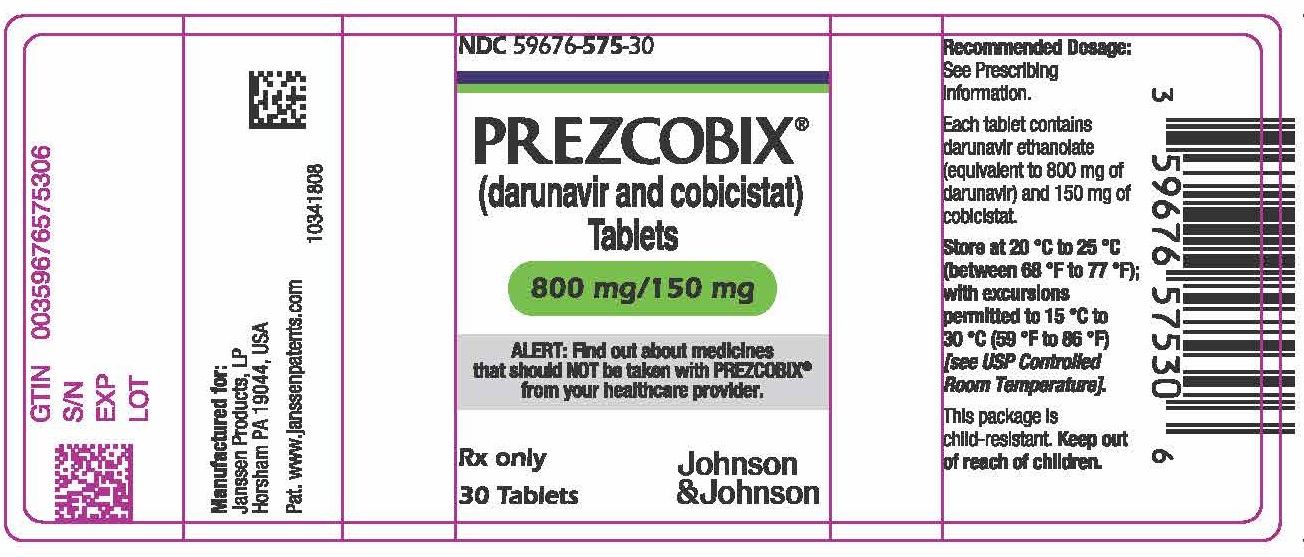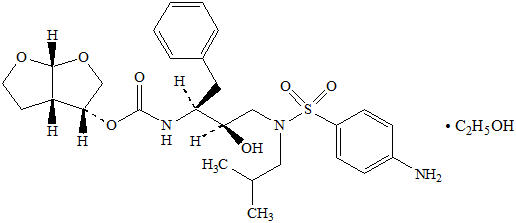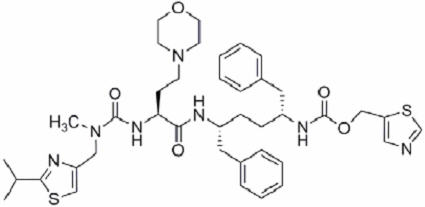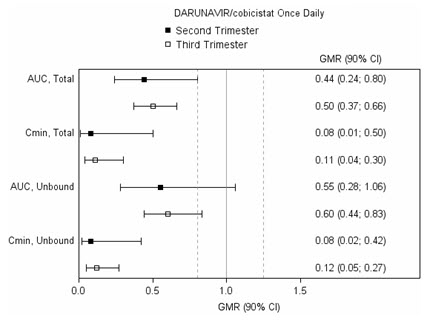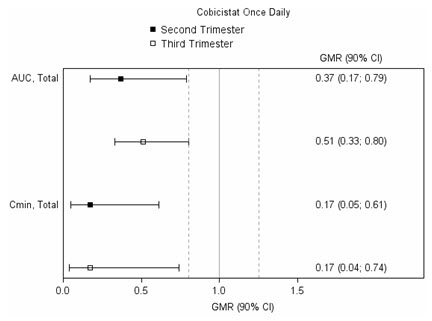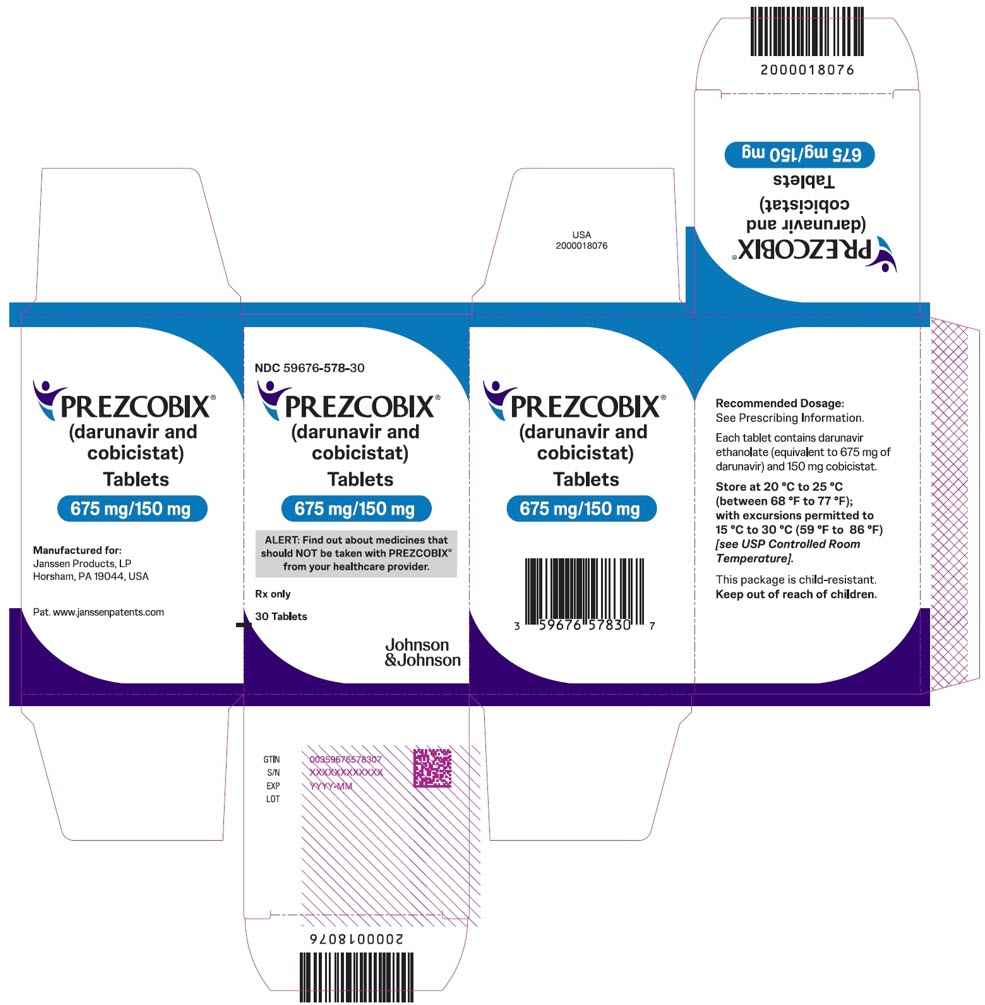 DRUG LABEL: PREZCOBIX
NDC: 59676-575 | Form: TABLET, FILM COATED
Manufacturer: Janssen Products LP
Category: prescription | Type: HUMAN PRESCRIPTION DRUG LABEL
Date: 20250408

ACTIVE INGREDIENTS: DARUNAVIR ETHANOLATE 800 mg/1 1; COBICISTAT 150 mg/1 1
INACTIVE INGREDIENTS: HYPROMELLOSE, UNSPECIFIED; MICROCRYSTALLINE CELLULOSE; SILICON DIOXIDE; CROSPOVIDONE (120 .MU.M); MAGNESIUM STEARATE; POLYVINYL ALCOHOL, UNSPECIFIED; TITANIUM DIOXIDE; POLYETHYLENE GLYCOL, UNSPECIFIED; TALC; FERRIC OXIDE RED; FERROSOFERRIC OXIDE

HIGHLIGHTS OF PRESCRIBING INFORMATION

These highlights do not include all the information needed to use PREZCOBIX safely and effectively. See full prescribing information for PREZCOBIX.
PREZCOBIX®(darunavir and cobicistat) tablets, for oral use
Initial U.S. Approval: 2015

RECENT MAJOR CHANGES

Indications and Usage (1) | 03/2025
Dosage and Administration (2.1) | 03/2025

1 INDICATIONS AND USAGE

PREZCOBIX is a two-drug combination of darunavir, a human immunodeficiency virus (HIV-1) protease inhibitor, and cobicistat, a CYP3A inhibitor, and is indicated for the treatment of HIV-1 in treatment-naïve and treatment-experienced adults and pediatric patients weighing at least 25 kg with no darunavir resistance-associated substitutions (V11I, V32I, L33F, I47V, I50V, I54L, I54M, T74P, L76V, I84V, L89V). (1)

2 DOSAGE AND ADMINISTRATION

Recommended dosage:

- Adults and pediatric patients weighing at least 40 kg: One 800 mg/150 mg tablet taken once daily with food. (2.1)
- Pediatric patients weighing at least 25 kg to less than 40 kg: One 675 mg/150 mg tablet taken once daily with food. (2.1)

Testing Prior to Initiation:HIV genotypic testing is recommended for antiretroviral treatment experienced patients. Assess estimated creatinine clearance in all patients prior to starting PREZCOBIX. When used with tenofovir DF: Assess urine glucose and urine protein at baseline and monitor creatinine clearance, urine glucose, and urine protein. Monitor serum phosphorus in patients with or at risk for renal impairment. (2.2)

3 DOSAGE FORMS AND STRENGTHS

- Tablets: 800 mg of darunavir and 150 mg of cobicistat. (3)
- Tablets: 675 mg of darunavir and 150 mg of cobicistat. (3)

4 CONTRAINDICATIONS

PREZCOBIX is contraindicated in patients receiving certain co-administered drugs for which altered plasma concentrations are associated with serious and/or life-threatening events or loss of therapeutic effect. (4, 7.2)

5 WARNINGS AND PRECAUTIONS

- Drug-induced hepatitis (e.g., acute hepatitis, cytolytic hepatitis), liver injury, including some fatalities can occur with PREZCOBIX. Monitor liver function before and during therapy, especially in patients with underlying chronic hepatitis, cirrhosis, or in patients who have pre-treatment elevations of transaminases. (5.1)
- Skin reactions ranging from mild to severe, including Stevens-Johnson Syndrome, toxic epidermal necrolysis, drug rash with eosinophilia and systemic symptoms and acute generalized exanthematous pustulosis, can occur with PREZCOBIX. Discontinue treatment if severe reaction develops. (5.2)
- When PREZCOBIX is used in combination with a tenofovir disoproxil fumarate (tenofovir DF) containing regimen, cases of acute renal failure and Fanconi syndrome have been reported. (5.4)
- PREZCOBIX is not recommended in combination with other antiretroviral drugs that require pharmacokinetic boosting. (5.6)
- Monitor in patients with a known sulfonamide allergy. (5.7)
- Patients receiving PREZCOBIX may develop new onset or exacerbations of diabetes mellitus/hyperglycemia (5.8), redistribution/accumulation of body fat (5.9), and immune reconstitution syndrome. (5.10)
- Patients with hemophilia may develop increased bleeding events. (5.11)

6 ADVERSE REACTIONS

- The most common adverse reactions to darunavir, a component of PREZCOBIX (incidence greater than or equal to 5%) of at least moderate severity (greater than or equal to Grade 2) were diarrhea, nausea, rash, headache, abdominal pain, and vomiting. (6.1)

To report SUSPECTED ADVERSE REACTIONS, contact Janssen Products, LP at 1-800-JANSSEN (1-800-526-7736) or FDA at 1-800-FDA-1088 or www.fda.gov/medwatch.

7 DRUG INTERACTIONS

- Co-administration of PREZCOBIX with other drugs can alter the concentration of other drugs and other drugs may alter the concentrations of darunavir or cobicistat. Consult the full prescribing information prior to and during treatment for potential drug interactions. (4, 5.6, 7, 12.3)

8 USE IN SPECIFIC POPULATIONS

- Pregnancy: PREZCOBIX is not recommended during pregnancy due to substantially lower exposures of darunavir and cobicistat during pregnancy. (8.1, 12.3)
- Lactation: Breastfeeding is not recommended. (8.2)
- Pediatrics: Not recommended for pediatric patients weighing less than 25 kg. (8.4)

FULL PRESCRIBING INFORMATION

1 INDICATIONS AND USAGE

PREZCOBIX is indicated in combination with other antiretroviral agents for the treatment of human immunodeficiency virus (HIV-1) in treatment-naïve and treatment-experienced adults and pediatric patients weighing at least 25 kg with no darunavir resistance-associated substitutions (V11I, V32I, L33F, I47V, I50V, I54L, I54M, T74P, L76V, I84V, L89V).

2 DOSAGE AND ADMINISTRATION

2.1 Recommended Dosage in Adults and Pediatric Patients Weighing at Least 25 kg

The recommended dosages of PREZCOBIX for adults and pediatric patients weighing at least 25 kg are shown in Table 1. The pediatric dose is based on weight. Administer PREZCOBIX orally with food in conjunction with other antiretroviral agents.

Table 1: Recommended Dosages of PREZCOBIX in Adults and Pediatric Patients Weighing at Least 25 kg, who are Treatment-Naïve or Treatment-Experienced Without DRV RAMs [DRV-resistance-associated mutations (RAMs): V11I, V32I, L33F, I47V, I50V, I54M, I54L, T74P, L76V, I84V, L89V.]
Patient Population | Dose (once daily with food)
Adult Patients | One 800 mg darunavir/150 mg cobicistat tablet
Pediatric Patients weighing at least 40 kg | One 800 mg darunavir/150 mg cobicistat tablet
Pediatric Patients weighing at least 25 kg to less than 40 kg | One 675 mg darunavir/150 mg cobicistat tablet

Before prescribing PREZCOBIX 675 mg/150 mg tablets, children should be assessed for the ability to swallow tablets. For patients unable to swallow the 675 mg/150 mg tablet whole, the scored tablet may be split by hand into two pieces. Each piece should be consumed immediately after splitting to ensure the entire dose is administered. The score line is only to facilitate breaking for ease of swallowing and not to divide into equal doses.

2.2 Testing Prior to Initiation of PREZCOBIX

HIV Genotypic Testing

HIV genotypic testing is recommended for antiretroviral treatment-experienced patients. However, when HIV genotypic testing is not feasible, PREZCOBIX can be used in protease inhibitor-naïve patients, but is not recommended in protease inhibitor-experienced patients.

Creatinine Clearance

Prior to starting PREZCOBIX, assess estimated creatinine clearance because cobicistat decreases estimated creatinine clearance due to inhibition of tubular secretion of creatinine without affecting actual renal glomerular function [see Warnings and Precautions (5.3)] . When co-administering PREZCOBIX with tenofovir disoproxil fumarate (tenofovir DF) assess estimated creatinine clearance, urine glucose, and urine protein at baseline [see Warnings and Precautions (5.4)] .

2.3 Not Recommended in Severe Renal Impairment

PREZCOBIX co-administered with tenofovir DF is not recommended in patients who have an estimated creatinine clearance below 70 mL per minute [see Warnings and Precautions (5.4) and Adverse Reactions (6.1)] .

2.4 Not Recommended in Severe Hepatic Impairment

PREZCOBIX is not recommended for use in patients with severe hepatic impairment [see Use in Specific Populations (8.6)and Clinical Pharmacology (12.3)] .

2.5 Not Recommended During Pregnancy

PREZCOBIX is not recommended during pregnancy because of substantially lower exposures of darunavir and cobicistat during the second and third trimesters [see Use in Specific Populations (8.1)and Clinical Pharmacology (12.3)] .

PREZCOBIX should not be initiated in pregnant individuals. An alternative regimen is recommended for those who become pregnant during therapy with PREZCOBIX.

3 DOSAGE FORMS AND STRENGTHS

PREZCOBIX 800 mg darunavir/150 mg cobicistat is a pink, oval-shaped, film-coated tablet debossed with “800” on one side and “TG” on the other side.

PREZCOBIX 675 mg darunavir/150 mg cobicistat is a green to dark green, oval-shaped, scored film-coated tablet debossed with “675” on one side and “TG” on the other side.

4 CONTRAINDICATIONS

Darunavir and cobicistat are both inhibitors of the cytochrome P450 3A (CYP3A) isoform. PREZCOBIX should not be co-administered with medicinal products that are highly dependent on CYP3A for clearance and for which increased plasma concentrations are associated with serious and/or life-threatening events (narrow therapeutic index). Darunavir and cobicistat are both substrates of the cytochrome P450 3A (CYP3A) isoform. Co-administration of PREZCOBIX with CYP3A inducers may lead to lower exposures of darunavir and cobicistat and potential loss of efficacy of darunavir and possible resistance. Examples of drugs that are contraindicated for co-administration with PREZCOBIX [see Drug Interactions (7.3)and Clinical Pharmacology (12.3)] are listed below.

- Alpha 1-adrenoreceptor antagonist: alfuzosin
- Anticonvulsants: carbamazepine, phenobarbital, phenytoin
- Anti-gout: colchicine, in patients with renal and/or hepatic impairment
- Antimycobacterial: rifampin
- Antipsychotics: lurasidone, pimozide
- Cardiac Disorders: dronedarone, ivabradine, ranolazine
- Ergot derivatives, e.g. dihydroergotamine, ergotamine, methylergonovine
- Herbal product: St. John's wort (Hypericum perforatum)
- Hepatitis C direct acting antiviral: elbasvir/grazoprevir
- Lipid modifying agents: lomitapide, lovastatin, simvastatin
- Opioid Antagonist: naloxegol
- PDE-5 inhibitor: sildenafil when used for treatment of pulmonary arterial hypertension
- Sedatives/hypnotics: orally administered midazolam, triazolam

5 WARNINGS AND PRECAUTIONS

5.1 Hepatotoxicity

During the darunavir clinical development program (N=3063), where darunavir was co-administered with ritonavir 100 mg once or twice daily, drug-induced hepatitis (e.g., acute hepatitis, cytolytic hepatitis) was reported in 0.5% of participants. Patients with pre-existing liver dysfunction, including chronic active hepatitis B or C, have an increased risk for liver function abnormalities including severe hepatic adverse reactions.

Post-marketing cases of liver injury, including some fatalities, have also been reported with darunavir co-administered with ritonavir. These have generally occurred in patients with advanced HIV-1 disease taking multiple concomitant medications, having co-morbidities including hepatitis B or C co-infection, and/or developing immune reconstitution syndrome. A causal relationship with darunavir co-administered with ritonavir has not been established.

Appropriate laboratory testing should be conducted prior to initiating therapy with PREZCOBIX and patients should be monitored during treatment. Increased AST/ALT monitoring should be considered in patients with underlying chronic hepatitis, cirrhosis, or in patients who have pre-treatment elevations of transaminases, especially during the first several months of PREZCOBIX treatment.

Evidence of new or worsening liver dysfunction (including clinically significant elevation of liver enzymes and/or symptoms such as fatigue, anorexia, nausea, jaundice, dark urine, liver tenderness, hepatomegaly) in patients on PREZCOBIX should prompt consideration of interruption or discontinuation of treatment.

5.2 Severe Skin Reactions

During the darunavir clinical development program (n=3063), where darunavir was co-administered with ritonavir 100 mg once or twice daily, severe skin reactions, accompanied by fever and/or elevations of transaminases in some cases, was reported in 0.4% of participants. Stevens-Johnson Syndrome was rarely (less than 0.1%) reported during the clinical development program. During post-marketing experience toxic epidermal necrolysis, drug rash with eosinophilia and systemic symptoms, and acute generalized exanthematous pustulosis have been reported. Discontinue PREZCOBIX immediately if signs or symptoms of severe skin reactions develop. These can include but are not limited to severe rash or rash accompanied with fever, general malaise, fatigue, muscle or joint aches, blisters, oral lesions, conjunctivitis, hepatitis and/or eosinophilia.

Mild-to-moderate rash was also reported and often occurred within the first four weeks of treatment and resolved with continued dosing.

5.3 Effects on Serum Creatinine

Cobicistat decreases estimated creatinine clearance due to inhibition of tubular secretion of creatinine without affecting actual renal glomerular function. This effect should be considered when interpreting changes in estimated creatinine clearance in patients initiating PREZCOBIX, particularly in patients with medical conditions or receiving drugs needing monitoring with estimated creatinine clearance.

Prior to initiating therapy with PREZCOBIX, assess estimated creatinine clearance [see Dosage and Administration (2.2)] . Dosage recommendations are not available for drugs that require dosage adjustments in PREZCOBIX-treated patients with renal impairment [see Drug Interactions (7.3) and Clinical Pharmacology (12.2)] . Consider alternative medications that do not require dosage adjustments in patients with renal impairment.

Although cobicistat may cause modest increases in serum creatinine and modest declines in estimated creatinine clearance without affecting renal glomerular function, patients who experience a confirmed increase in serum creatinine of greater than 0.4 mg/dL from baseline should be closely monitored for renal safety.

5.4 New Onset or Worsening Renal Impairment When Used With Tenofovir Disoproxil Fumarate

Renal impairment, including cases of acute renal failure and Fanconi syndrome, has been reported when cobicistat, a component of PREZCOBIX, was used in an antiretroviral regimen that contained tenofovir DF. Co-administration of PREZCOBIX and tenofovir DF is not recommended in patients who have an estimated creatinine clearance below 70 mL/min [see Dosage and Administration (2.3)] .

- Document urine glucose and urine protein at baseline [see Dosage and Administration (2.2)] and perform routine monitoring of estimated creatinine clearance, urine glucose, and urine protein during treatment when PREZCOBIX is used with tenofovir DF. Measure serum phosphorus in patients with or at risk for renal impairment when used with tenofovir DF.
- Co-administration of PREZCOBIX and tenofovir DF in combination with concomitant or recent use of a nephrotoxic agent is not recommended.

See cobicistat full prescribing information for additional information regarding cobicistat.

5.5 Risk of Serious Adverse Reactions or Loss of Virologic Response Due to Drug Interactions

Initiation of PREZCOBIX, which inhibits CYP3A, in patients receiving medications metabolized by CYP3A, or initiation of medications metabolized by CYP3A in patients already receiving PREZCOBIX may increase plasma concentrations of medications metabolized by CYP3A and reduce plasma concentrations of active metabolite(s) formed by CYP3A. Initiation of medications that inhibit or induce CYP3A may respectively increase or decrease concentrations of PREZCOBIX.

These interactions may lead to:

- clinically significant adverse reactions, potentially leading to severe, life threatening, or fatal events from higher exposures of concomitant medications.
- clinically significant adverse reactions from higher exposures of PREZCOBIX.
- loss of therapeutic effect of the concomitant medications from lower exposures of active metabolite(s).
- loss of therapeutic effect of PREZCOBIX and possible development of resistance from lower exposures of PREZCOBIX.

See Table 2 for steps to prevent or manage these possible and known significant drug interactions, including dosing recommendations. Consider the potential for drug interactions prior to and during PREZCOBIX therapy; review concomitant medications during PREZCOBIX therapy; and monitor for the adverse reactions associated with concomitant medications [see Contraindications (4) and Drug Interactions (7)] .

When used with concomitant medications, PREZCOBIX may result in different drug interactions than those observed or expected with darunavir co-administered with ritonavir. Complex or unknown mechanisms of drug interactions preclude extrapolation of drug interactions with darunavir co-administered with ritonavir to certain PREZCOBIX interactions [see Drug Interactions (7) and Clinical Pharmacology (12.3)] .

5.6 Antiretrovirals Not Recommended

PREZCOBIX is not recommended in combination with other antiretroviral drugs that require pharmacokinetic boosting (i.e., another protease inhibitor or elvitegravir) because dosing recommendations for such combinations have not been established and co-administration may result in decreased plasma concentrations of the antiretroviral agents, leading to loss of therapeutic effect and development of resistance.

PREZCOBIX is not recommended in combination with products containing the individual components of PREZCOBIX (darunavir and cobicistat) or with ritonavir. For additional recommendations on use of PREZCOBIX with other antiretroviral agents, [see Drug Interactions (7)] .

5.7 Sulfa Allergy

Darunavir contains a sulfonamide moiety. Monitor patients with a known sulfonamide allergy after initiating PREZCOBIX. In clinical studies with darunavir co-administered with ritonavir, the incidence and severity of rash were similar in subjects with or without a history of sulfonamide allergy.

5.8 Diabetes Mellitus/Hyperglycemia

New onset diabetes mellitus, exacerbation of pre-existing diabetes mellitus, and hyperglycemia have been reported during postmarketing surveillance in patients with HIV-1 receiving HIV protease inhibitor (PI) therapy. Some patients required either initiation or dose adjustments of insulin or oral hypoglycemic agents for treatment of these events. In some cases, diabetic ketoacidosis has occurred. In those patients who discontinued PI therapy, hyperglycemia persisted in some cases. Because these events have been reported voluntarily during clinical practice, estimates of frequency cannot be made and causal relationships between HIV PI therapy and these events have not been established.

5.9 Fat Redistribution

Redistribution/accumulation of body fat, including central obesity, dorsocervical fat enlargement (buffalo hump), peripheral wasting, facial wasting, breast enlargement, and "cushingoid appearance" have been observed in patients receiving antiretroviral therapy. The mechanism and long-term consequences of these events are currently unknown. A causal relationship has not been established.

5.10 Immune Reconstitution Syndrome

Immune reconstitution syndrome has been reported in patients treated with combination antiretroviral therapy, including PREZCOBIX. During the initial phase of combination antiretroviral treatment, patients whose immune systems respond may develop an inflammatory response to indolent or residual opportunistic infections (such as Mycobacterium avium infection, cytomegalovirus, Pneumocystis jirovecii pneumonia [PCP], or tuberculosis), which may necessitate further evaluation and treatment.

Autoimmune disorders (such as Graves' disease, polymyositis, Guillain-Barré syndrome and autoimmune hepatitis) have also been reported to occur in the setting of immune reconstitution; however, the time to onset is more variable, and can occur many months after initiation of antiretroviral treatment.

5.11 Hemophilia

There have been reports of increased bleeding, including spontaneous skin hematomas and hemarthrosis in patients with hemophilia type A and B treated with HIV PIs. In some patients, additional factor VIII was given. In more than half of the reported cases, treatment with HIV PIs was continued or reintroduced if treatment had been discontinued. A causal relationship between PI therapy and these episodes has not been established.

6 ADVERSE REACTIONS

The following adverse reactions are discussed in other sections of the labeling:

- Hepatotoxicity [see Warnings and Precautions (5.1)]
- Severe skin reactions [see Warnings and Precautions (5.2)]
- Effects on serum creatinine [see Warnings and Precautions (5.3)]
- New onset or worsening renal impairment when used with tenofovir DF [see Warnings and Precautions (5.4)]
- Immune Reconstitution Syndrome [see Warnings and Precautions (5.10)]

6.1 Clinical Trials Experience

Because clinical trials are conducted under widely varying conditions, adverse reaction rates observed in the clinical trials of a drug cannot be directly compared to rates in the clinical trials of another drug and may not reflect the rates observed in clinical practice.

Clinical Trials in Adults

During the darunavir clinical development program, where darunavir was co-administered with ritonavir 100 mg once or twice daily, the most common clinical adverse reactions (incidence greater than or equal to 5%) of at least moderate intensity (greater than or equal to Grade 2) were diarrhea, nausea, rash, headache, abdominal pain, and vomiting. See the darunavir full prescribing information for additional information on adverse reactions reported with darunavir co-administered with ritonavir. See cobicistat full prescribing information for clinical trial information on adverse reactions reported with cobicistat.

One single arm clinical trial was conducted with darunavir and cobicistat administered as single entities in 313 participants with HIV-1. Adverse reactions evaluated through Week 24 did not differ substantially from those reported in clinical trials with darunavir co-administered with ritonavir.

Clinical Trials in Pediatrics

No clinical trials with PREZCOBIX were performed in pediatric patients. However, the safety of the components of PREZCOBIX, darunavir and cobicistat, co-administered with two nucleoside reverse transcriptase inhibitors, was evaluated in pediatric participants of 12 to less than 18 years of age with HIV-1 through clinical trial GS-US-216-0128 (Cohort 1, virologically-suppressed, N=7 with weight ≥40 kg) and pediatric participants 6 to less than 12 years of age (Cohort 2, virologically-suppressed, N=8 with weight ≥25 kg) through Week 48. Safety analyses of this trial in these pediatric participants did not identify new safety concerns compared to the known safety profile of PREZCOBIX in adult participants [see Clinical Studies (14.2)] .

6.2 Postmarketing Experience

The following adverse reactions have been identified during post-approval use of darunavir. Because these reactions are reported voluntarily from a population of uncertain size, it is not always possible to reliably estimate their frequency or establish a causal relationship to drug exposure.

Metabolism and Nutrition Disorders

Redistribution of body fat

Musculoskeletal and Connective Tissue Disorders

Rhabdomyolysis (associated with co-administration with HMG-CoA reductase inhibitors)

Renal and Urinary Disorders

Crystal nephropathy, crystalluria

Skin and Subcutaneous Tissue Disorders

Toxic epidermal necrolysis, acute generalized exanthematous pustulosis, drug rash with eosinophilia and systemic symptoms [see Warnings and Precautions (5.2)] .

7 DRUG INTERACTIONS

7.1 Potential for PREZCOBIX to Affect Other Drugs

Darunavir co-administered with cobicistat is an inhibitor of CYP3A and CYP2D6. Cobicistat inhibits the following transporters: P-glycoprotein (P-gp), BCRP, MATE1, OATP1B1 and OATP1B3. Therefore, co-administration of PREZCOBIX with drugs that are primarily metabolized by CYP3A and/or CYP2D6 or are substrates of P-gp, BCRP, MATE1, OATP1B1 or OATP1B3 may result in increased plasma concentrations of such drugs, which could increase or prolong their therapeutic effect and can be associated with adverse events. Co-administration of PREZCOBIX with drugs that have active metabolite(s) formed by CYP3A may result in reduced plasma concentrations of these active metabolite(s), potentially leading to loss of their therapeutic effect (see Table 2).

7.2 Potential for Other Drugs to Affect PREZCOBIX

Darunavir is metabolized by CYP3A. Cobicistat is metabolized by CYP3A, and to a minor extent, by CYP2D6. Co-administration of PREZCOBIX and drugs that induce CYP3A activity are expected to increase the clearance of darunavir and cobicistat, resulting in lowered plasma concentrations of darunavir and cobicistat which may lead to loss of therapeutic effect and development of resistance. Co-administration of PREZCOBIX and other drugs that inhibit CYP3A may result in increased plasma concentrations of darunavir and cobicistat (see Table 2).

7.3 Established and Other Potentially Significant Drug Interactions

Table 2 provides dosing recommendations for expected clinically relevant interactions with PREZCOBIX (this table is not all inclusive). These recommendations are based on either drug interaction trials or predicted interactions due to the expected magnitude of interaction and potential for serious adverse events or loss of therapeutic effect. The table includes examples of potentially significant interactions but is not all inclusive , and therefore the label of each drug that is co-administered with PREZCOBIX should be consulted for information related to the route of metabolism, interaction pathways, potential risks, and specific actions to be taken with regard to co-administration. For the list of examples of contraindicated drugs, [see Contraindications (4)] .

Table 2: Established and Other Potentially Significant [this table is not all inclusive] Drug Interactions: Alterations in Dose or Regimen May Be Recommended
Concomitant Drug Class: Drug Name Examples | Effect on Concentration of Darunavir, Cobicistat, or Concomitant Drug | Clinical Comment
HIV-1 antiviral agents: Nucleoside Reverse Transcriptase Inhibitors (NRTIs)
didanosine | ↔ darunavir ↔ cobicistat ↔ didanosine | Didanosine should be administered one hour before or two hours after PREZCOBIX (administered with food).
HIV-1 antiviral agents: Non-Nucleoside Reverse Transcriptase Inhibitors (NNRTIs)
efavirenz | ↓ cobicistat ↓ darunavir | Co-administration with efavirenz is not recommended because it may result in loss of therapeutic effect and development of resistance to darunavir.
etravirine | ↓ cobicistat darunavir: effect unknown | Co-administration with etravirine is not recommended because it may result in loss of therapeutic effect and development of resistance to darunavir.
nevirapine | ↓ cobicistat darunavir: effect unknown | Co-administration with nevirapine is not recommended because it may result in loss of therapeutic effect and development of resistance to darunavir.
HIV-1 antiviral agents: CCR5 co-receptor antagonists
maraviroc | ↑ maraviroc | Maraviroc is a substrate of CYP3A. When co-administered with PREZCOBIX, patients should receive maraviroc 150 mg twice daily.
Other agents
Alpha 1-adrenoreceptor antagonist: alfuzosin | ↑ alfuzosin | Co-administration is contraindicated due to potential for serious and/or life-threatening reactions such as hypotension.
Antibacterials: clarithromycin, erythromycin, telithromycin | ↑ darunavir ↑ cobicistat ↑ antibacterial | Consider alternative antibiotics with concomitant use of PREZCOBIX.
Anticancer agents: dasatinib, nilotinib | ↑ anticancer agent | A decrease in the dosage or an adjustment of the dosing interval of dasatinib or nilotinib may be necessary when co-administered with PREZCOBIX. Consult the dasatinib and nilotinib prescribing information for dosing instructions.
vinblastine, vincristine |  | For vincristine and vinblastine, consider temporarily withholding the cobicistat-containing antiretroviral regimen in patients who develop significant hematologic or gastrointestinal side effects when PREZCOBIX is administered concurrently with vincristine or vinblastine. If the antiretroviral regimen must be withheld for a prolonged period, consider initiating a revised regimen that does not include a CYP3A or P-gp inhibitor.
Anticoagulants: Direct Oral Anticoagulants (DOACs) apixaban | ↑ apixaban | Due to potentially increased bleeding risk, dosing recommendations for co-administration of apixaban with PREZCOBIX depend on the apixaban dose. Refer to apixaban dosing instructions for co-administration with P-gp and strong CYP3A inhibitors in apixaban prescribing information.
rivaroxaban | ↑ rivaroxaban | Co-administration of rivaroxaban with PREZCOBIX is not recommended because it may lead to an increased bleeding risk.
dabigatran etexilate edoxaban | ↑ dabigatran ↑ edoxaban | Refer to the dabigatran etexilate or edoxaban prescribing information for recommendations regarding co-administration. The specific recommendations are based on indication, renal function, and effect of the co-administered P-gp inhibitors on the concentration of dabigatran or edoxaban. Clinical monitoring is recommended when a DOAC not affected by CYP3A4 but transported by P-gp, including dabigatran etexilate and edoxaban, is co-administered with PREZCOBIX.
Other Anticoagulants:
warfarin | warfarin: effect unknown | Monitor the international normalized ratio (INR) when co-administering with warfarin.
Anticonvulsants: carbamazepine, phenobarbital, phenytoin | ↓ darunavir ↓ cobicistat | Co-administration is contraindicated due to potential for reduced plasma concentrations of darunavir, which may result in loss of therapeutic effect and development of resistance.
Anticonvulsants with CYP3A induction effects that are NOT contraindicated: e.g. eslicarbazepine, oxcarbazepine | ↓ cobicistat darunavir: effect unknown | Consider alternative anticonvulsant or antiretroviral therapy to avoid potential changes in exposures. If co-administration is necessary, monitor for lack or loss of virologic response.
Anticonvulsants that are metabolized by CYP3A: e.g. clonazepam | ↑ clonazepam | Clinical monitoring of anticonvulsants is recommended.
Antidepressants: Selective Serotonin Reuptake Inhibitors (SSRIs): e.g. paroxetine, sertraline | SSRIs: effects unknown | When co-administering with SSRIs, TCAs, or trazodone, careful dose titration of the antidepressant to the desired effect, including using the lowest feasible initial or maintenance dose, and monitoring for antidepressant response are recommended.
Tricyclic Antidepressants (TCAs): e.g. amitriptyline, desipramine, imipramine, nortriptyline | ↑ TCAs | When co-administering with SSRIs, TCAs, or trazodone, careful dose titration of the antidepressant to the desired effect, including using the lowest feasible initial or maintenance dose, and monitoring for antidepressant response are recommended.
Other antidepressants: trazodone | ↑ trazodone | When co-administering with SSRIs, TCAs, or trazodone, careful dose titration of the antidepressant to the desired effect, including using the lowest feasible initial or maintenance dose, and monitoring for antidepressant response are recommended.
Antifungals: itraconazole, isavuconazole, ketoconazole, posaconazole | ↑ darunavir ↑ cobicistat | Monitor for increased darunavir or cobicistat and/or antifungal adverse reactions.
Antifungals: itraconazole, isavuconazole, ketoconazole, posaconazole | ↑ itraconazole ↑ ketoconazole ↑ isavuconazole ↔ posaconazole | Specific dosing recommendations are not available for co-administration with these antifungals. Monitor for increased itraconazole or ketoconazole adverse reactions.
voriconazole | voriconazole: effects unknown | Co-administration with voriconazole is not recommended unless benefit/risk assessment justifies the use of voriconazole.
Anti-gout: colchicine | ↑ colchicine | Co-administration is contraindicated in patients with renal and/or hepatic impairment due to potential for serious and/or life-threatening reactions. For patients without renal or hepatic impairment:; - Treatment of gout flares – co-administration of colchicine: 0.6 mg (1 tablet) × 1 dose, followed by 0.3 mg (half tablet) 1 hour later. Treatment course to be repeated no earlier than 3 days. - Prophylaxis of gout flares – co-administration of colchicine: If the original regimen was 0.6 mg twice a day, the regimen should be adjusted to 0.3 mg once a day. If the original regimen was 0.6 mg once a day, the regimen should be adjusted to 0.3 mg once every other day. - Treatment of familial Mediterranean fever – co-administration of colchicine: Maximum daily dose of 0.6 mg (may be given as 0.3 mg twice a day).
Antimalarial: artemether/lumefantrine | artemether: effect unknown lumefantrine: effect unknown | Monitor for a potential decrease of antimalarial efficacy or potential QT prolongation.
Antimycobacterials:
rifampin | ↓ darunavir ↓ cobicistat | Co-administration is contraindicated due to potential for loss of therapeutic effect and development of resistance.
rifabutin | ↑ rifabutin cobicistat: effects unknown darunavir: effects unknown | When used in combination with PREZCOBIX, the recommended dose of rifabutin is 150 mg every other day. Monitor for rifabutin-associated adverse reactions including neutropenia and uveitis.
rifapentine | ↓ darunavir | Co-administration with rifapentine is not recommended.
Antipsychotics: lurasidone | ↑ lurasidone | Co-administration is contraindicated due to potential for serious and/or life-threatening reactions.
pimozide | ↑ pimozide | Co-administration is contraindicated due to potential for serious and/or life-threatening reactions such as cardiac arrhythmias.
e.g. perphenazine, risperidone, thioridazine | ↑ antipsychotic | A decrease in the dose of antipsychotics that are metabolized by CYP3A or CYP2D6 may be needed when co-administered with PREZCOBIX.
quetiapine | ↑ quetiapine | Initiation of PREZCOBIX in patients taking quetiapine: Consider alternative antiretroviral therapy to avoid increases in quetiapine exposure. If co-administration is necessary, reduce the quetiapine dose to 1/6 of the current dose and monitor for quetiapine- associated adverse reactions. Refer to the quetiapine prescribing information for recommendations on adverse reaction monitoring. Initiation of quetiapine in patients taking PREZCOBIX: Refer to the quetiapine prescribing information for initial dosing and titration of quetiapine.
β-Blockers: e.g. carvedilol, metoprolol, timolol | ↑ beta-blockers | Clinical monitoring is recommended for co-administration with beta-blockers that are metabolized by CYP2D6.
Calcium channel blockers: e.g. amlodipine, diltiazem, felodipine, nifedipine, verapamil | ↑ calcium channel blockers | Clinical monitoring is recommended for co-administration with calcium channel blockers metabolized by CYP3A.
Cardiac Disorders:
ranolazine, ivabradine | ↑ ranolazine ↑ ivabradine | Co-administration is contraindicated due to potential for serious and/or life-threatening reactions.
dronedarone | ↑ dronedarone | Co-administration is contraindicated due to potential for serious and/or life-threatening reactions such as cardiac arrhythmias.
Other antiarrhythmics
e.g. amiodarone, disopyramide, flecainide, lidocaine (systemic), mexiletine, propafenone, quinidine | ↑ antiarrhythmics | Clinical monitoring is recommended upon co-administration with antiarrhythmics.
digoxin | ↑ digoxin | When co-administering with digoxin, titrate the digoxin dose and monitor digoxin concentrations.
Corticosteroids: dexamethasone (systemic) Corticosteroids primarily metabolized by CYP3A: e.g. betamethasone budesonide ciclesonide fluticasone methylprednisolone mometasone triamcinolone | ↓ darunavir ↓ cobicistat ↑ corticosteroids | Co-administration with systemic dexamethasone or other systemic corticosteroids that induce CYP3A may result in loss of therapeutic effect and development of resistance to PREZCOBIX. Consider alternative corticosteroids. Co-administration with corticosteroids (all routes of administration) of which exposures are significantly increased by strong CYP3A inhibitors can increase the risk for Cushing's syndrome and adrenal suppression. Alternative corticosteroids including beclomethasone, prednisone and prednisolone (for which PK and/or PD are less affected by strong CYP3A inhibitors relative to other steroids) should be considered, particularly for long-term use.
Endothelin receptor antagonists: bosentan | ↓ darunavir ↓ cobicistat ↑ bosentan | Initiation of bosentan in patients taking PREZCOBIX: In patients who have been receiving PREZCOBIX for at least 10 days, start bosentan at 62.5 mg once daily or every other day based upon individual tolerability. Initiation of PREZCOBIX in patients on bosentan: Discontinue use of bosentan at least 36 hours prior to initiation of PREZCOBIX. After at least 10 days following the initiation of PREZCOBIX, resume bosentan at 62.5 mg once daily or every other day based upon individual tolerability. Switching from darunavir co-administered with ritonavir to PREZCOBIX in patients on bosentan: Maintain bosentan dose.
Ergot derivatives: e.g. dihydroergotamine, ergotamine, methylergonovine | ↑ ergot derivatives | Co-administration is contraindicated due to potential for serious and/or life-threatening reactions such as acute ergot toxicity characterized by peripheral vasospasm and ischemia of the extremities and other tissues.
Hepatitis C virus (HCV): Direct-Acting Antivirals: elbasvir/grazoprevir | ↑ elbasvir/grazoprevir | Co-administration is contraindicated due to potential for the increased risk of alanine transaminase (ALT) elevations.
glecaprevir/pibrentasvir | ↑ glecaprevir ↑ pibrentasvir | Co-administration of PREZCOBIX with glecaprevir/pibrentasvir is not recommended.
Herbal product: St. John's wort (Hypericum perforatum) | ↓ darunavir ↓ cobicistat | Co-administration is contraindicated due to potential for reduced plasma concentrations of darunavir, which may result in loss of therapeutic effect and development of resistance.
Hormonal contraceptives: |  | Additional or alternative (non-hormonal) forms of contraception should be considered when estrogen-containing contraceptives are co-administered with PREZCOBIX [see Use in Specific Populations (8.3)] .
drospirenone/ethinylestradiol | ↑ drospirenone ↓ ethinylestradiol | For co-administration with drospirenone, clinical monitoring is recommended due to the potential for hyperkalemia.
Other progestin/estrogen contraceptives | progestin: effects unknown estrogen: effects unknown | No data are available to make recommendations on co-administration with other hormonal contraceptives.
Immunosuppressants: cyclosporine, sirolimus, tacrolimus | ↑ immunosuppressants | These immunosuppressant agents are metabolized by CYP3A. Therapeutic drug monitoring is recommended with concomitant use
Immunosuppressant /neoplastic: everolimus | ↑ immunosuppressants | Co-administration of everolimus and PREZCOBIX is not recommended.
irinotecan |  | Discontinue PREZCOBIX at least 1 week prior to starting irinotecan therapy. Do not administer PREZCOBIX with irinotecan unless there are no therapeutic alternatives.
Inhaled beta agonist: salmeterol | ↑ salmeterol | Co-administration with salmeterol is not recommended and may result in increased risk of cardiovascular adverse events associated with salmeterol, including QT prolongation, palpitations, and sinus tachycardia.
Lipid Modifying Agents
HMG-CoA reductase inhibitors: lovastatin, simvastatin | ↑ lovastatin ↑ simvastatin | Co-administration is contraindicated due to potential for serious reactions such as myopathy including rhabdomyolysis.
atorvastatin, fluvastatin, pitavastatin, pravastatin, rosuvastatin | ↑ atorvastatin ↑ fluvastatin ↑ pravastatin ↑ rosuvastatin pitavastatin: effect unknown | For atorvastatin, fluvastatin, pitavastatin, pravastatin, and rosuvastatin, start with the lowest recommended dose and titrate while monitoring for safety (e.g. myopathy). Dosage recommendations with atorvastatin or rosuvastatin are as follows:; - atorvastatin dosage should not exceed 20 mg/day - rosuvastatin dosage should not exceed 20 mg/day
Other lipid modifying agents: lomitapide | ↑ lomitapide | Co-administration is contraindicated due to potential for markedly increased transaminases associated with increased plasma concentrations of lomitapide.
Narcotic analgesics metabolized by CYP3A: e.g. fentanyl, oxycodone | ↑ fentanyl ↑ oxycodone | Careful monitoring of therapeutic effects and adverse reactions associated with CYP3A-metabolized narcotic analgesics (including potentially fatal respiratory depression) is recommended with co-administration.
tramadol | ↑ tramadol | A dose decrease may be needed for tramadol with concomitant use.
Narcotic analgesic for treatment of opioid dependence: buprenorphine, buprenorphine/naloxone, methadone | buprenorphine or buprenorphine/ naloxone: effects unknown methadone: effects unknown | Initiation of buprenorphine, buprenorphine/naloxone or methadone in patients taking PREZCOBIX: Carefully titrate the dose of buprenorphine, buprenorphine/naloxone or methadone to the desired effect; use the lowest feasible initial or maintenance dose. Initiation of PREZCOBIX in patients taking buprenorphine, buprenorphine/naloxone or methadone: A dose adjustment for buprenorphine, buprenorphine/naloxone or methadone may be needed. Monitor clinical signs and symptoms.
Opioid Antagonist
naloxegol | ↑ naloxegol | Co-administration of PREZCOBIX and naloxegol is contraindicated due to potential for precipitating opioid withdrawal symptoms.
Phosphodiesterase PDE-5 inhibitors: e.g. avanafil, sildenafil, tadalafil, vardenafil | ↑ PDE-5 inhibitors | Co-administration with avanafil is not recommended because a safe and effective avanafil dosage regimen has not been established. Co-administration with PDE-5 inhibitors may result in an increase in PDE-5 inhibitor-associated adverse reactions including hypotension, syncope, visual disturbances and priapism. Use of PDE-5 inhibitors for pulmonary arterial hypertension (PAH): Co-administration with sildenafil used for PAH is contraindicated due to potential for sildenafil associated adverse reactions (which include visual disturbances, hypotension, prolonged erection, and syncope). The following dose adjustments are recommended for use of tadalafil with PREZCOBIX:; - Initiation of tadalafil in patients taking PREZCOBIX: In patients receiving PREZCOBIX for at least one week, start tadalafil at 20 mg once daily. Increase to 40 mg once daily based upon individual tolerability. - Initiation of PREZCOBIX in patients taking tadalafil: Avoid use of tadalafil during the initiation of PREZCOBIX. Stop tadalafil at least 24 hours prior to starting PREZCOBIX. After at least one week following the initiation of PREZCOBIX, resume tadalafil at 20 mg once daily. Increase to 40 mg once daily based upon individual tolerability. - Patients switching from darunavir co-administered with ritonavir to PREZCOBIX: Maintain tadalafil dose.; Use of PDE-5 inhibitors for erectile dysfunction: Sildenafil at a single dose not exceeding 25 mg in 48 hours, vardenafil at a single dose not exceeding 2.5 mg dose in 72 hours, or tadalafil at a single dose not exceeding 10 mg dose in 72 hours can be used with increased monitoring for PDE-5 inhibitor-associated adverse reactions.
Platelet aggregation inhibitor:
ticagrelor | ↑ ticagrelor | Co-administration of PREZCOBIX and ticagrelor is not recommended.
clopidogrel | ↓ clopidogrel active metabolite | Co-administration of PREZCOBIX with clopidogrel is not recommended due to the potential reduction of the antiplatelet activity of clopidogrel.
prasugrel | ↔ prasugrel active metabolite | No dose adjustment is needed when prasugrel is co-administered with PREZCOBIX.
Sedatives/hypnotics: orally administered midazolam, triazolam | ↑ midazolam ↑ triazolam | Co-administration is contraindicated due to potential for serious and/or life-threatening reactions such as prolonged or increased sedation or respiratory depression. Triazolam and orally administered midazolam are extensively metabolized by CYP3A. Co-administration of triazolam or orally administered midazolam with PREZCOBIX may cause large increases in the concentrations of these benzodiazepines.
metabolized by CYP3A: e.g. buspirone, diazepam, estazolam, zolpidem | ↑ sedatives/hypnotics | With concomitant use, titration is recommended with sedatives/hypnotics metabolized by CYP3A and a lower dose of the sedatives/hypnotics should be considered with monitoring for increased and prolonged effects or adverse reactions.
parenterally administered midazolam |  | Co-administration of parenteral midazolam should be done in a setting that ensures close clinical monitoring and appropriate medical management in case of respiratory depression and/or prolonged sedation. Dose reduction for parenteral midazolam should be considered, especially if more than a single dose of midazolam is administered.
Urinary antispasmodics
fesoterodine | ↑ fesoterodine | When fesoterodine is co-administered with PREZCOBIX, do not exceed a fesoterodine dose of 4 mg once daily.
solifenacin | ↑ solifenacin | When solifenacin is co-administered with PREZCOBIX, do not exceed a solifenacin dose of 5 mg once daily.

7.4 Drugs without Clinically Significant Interactions with PREZCOBIX

Clinically relevant drug-drug interactions have not been observed or are not anticipated with concomitant use of darunavir and cobicistat with rilpivirine, dolutegravir, raltegravir, abacavir, emtricitabine, emtricitabine/tenofovir alafenamide, tenofovir DF, lamivudine, stavudine, zidovudine, or acid modifying medications (antacids, H2-receptor antagonists, proton pump inhibitors).

8 USE IN SPECIFIC POPULATIONS

8.1 Pregnancy

Pregnancy Exposure Registry

There is a pregnancy exposure registry that monitors pregnancy outcomes in individuals exposed to PREZCOBIX during pregnancy. Healthcare providers are encouraged to register patients by calling the Antiretroviral Pregnancy Registry (APR) 1-800-258-4263.

Risk Summary

PREZCOBIX is not recommended during pregnancy because of substantially lower exposures of darunavir and cobicistat during the second and third trimesters [see Dosage and Administration (2.5)] . A study evaluating the pharmacokinetics of antiretrovirals during pregnancy demonstrated substantially lower exposures of darunavir and cobicistat in the second and third trimesters compared to the post-partum period (see Data) and [see Clinical Pharmacology (12.3)].

Prospective pregnancy data from the APR are not sufficient to adequately assess the risk of birth defects or miscarriage. However, available data from the APR show no statistically significant difference in the overall risk of major birth defects for darunavir and cobicistat compared with the background rate for major birth defects of 2.7% in a U.S. reference population of the Metropolitan Atlanta Congenital Defects Program (MACDP) (see Data) . The rate of miscarriage is not reported in the APR. The estimated background rate of miscarriage in clinically recognized pregnancies in the U.S. general population is 15–20%. The background risk of major birth defects and miscarriage for the indicated population is unknown.

In animal reproduction studies, no adverse developmental effects were observed when the components of PREZCOBIX were administered separately at darunavir exposures less than 1 (mice and rabbits) and 3-times (rats), and at cobicistat exposures 1.6 (rats) and 3.8 (rabbits) times human exposures at the recommended daily dose of these components in PREZCOBIX (see Data) . No adverse developmental effects were seen when cobicistat was administered to rats through lactation at cobicistat exposures up to 1.2 times the human exposure at the recommended therapeutic dose.

Clinical Considerations

Not Recommended During Pregnancy

PREZCOBIX is not recommended for use during pregnancy because of substantially lower exposures of darunavir and cobicistat during pregnancy (see Data) and [see Clinical Pharmacology (12.3)] .

PREZCOBIX should not be initiated in pregnant individuals. An alternative regimen is recommended for individuals who become pregnant during therapy with PREZCOBIX.

Data

Human Data

PREZCOBIX in combination with a background regimen was evaluated in a clinical trial of 7 pregnant participants taking PREZCOBIX prior to enrollment and who were willing to remain on PREZCOBIX throughout the study. The study period included the second and third trimesters, and through 12 weeks postpartum. Six pregnant participants completed the trial.

Exposure to darunavir and cobicistat as part of an antiretroviral regimen was substantially lower during the second and third trimesters of pregnancy compared with postpartum [see Clinical Pharmacology (12.3)] .

One out of 6 pregnant participants who completed the study experienced virologic failure with HIV-1 RNA >1,000 copies/mL from the third trimester visit through the postpartum period. Five pregnant participants had sustained virologic response (HIV RNA <50 copies/mL) throughout the study period. There are no clinical data on the virologic response when PREZCOBIX is initiated during pregnancy.

Prospective reports from the APR of overall major birth defects in pregnancies exposed to the components of PREZCOBIX are compared with a U.S. background major birth defect rate. Methodological limitations of the APR include the use of MACDP as the external comparator group. Limitations of using an external comparator include differences in methodology and populations, as well as confounding due to the underlying disease.

There were no new clinically relevant safety findings compared with the known safety profile of PREZCOBIX in adults with HIV-1.

Darunavir: Based on prospective reports to the APR of over 980 exposures to darunavir-containing regimens during pregnancy resulting in live births (including over 660 exposed in the first trimester and over 320 exposed in the second/third trimester), the prevalence of birth defects in live births was 3.6% (95% CI: 2.3% to 5.3%) with first trimester exposure to darunavir-containing regimens and 2.5% (95% CI: 1.1% to 4.8%) with second/third trimester exposure to darunavir-containing regimens.

Cobicistat: Based on prospective reports to the APR of over 570 exposures to cobicistat-containing regimens during pregnancy resulting in live births (including over 480 exposed in the first trimester and over 80 exposed in the second/third trimester), the prevalence of birth defects in live births was 3.7% (95% CI: 2.2% to 5.7%) and 1.1% (95% CI: 0.0% to 6.2%) with first and second/third trimester, respectively, to cobicistat-containing regimens.

Animal Data

Darunavir: Reproduction studies conducted with darunavir showed no embryotoxicity or teratogenicity in mice (doses up to 1000 mg/kg from gestation day (GD) 6–15 with darunavir alone) and rats (doses up to 1000 mg/kg from GD 7–19 in the presence or absence of ritonavir) as well as in rabbits (doses up to 1000 mg/kg/day from GD 8–20 with darunavir alone). In these studies, darunavir exposures (based on AUC) were higher in rats (3-fold), whereas in mice and rabbits, exposures were lower (less than 1-fold) compared to those obtained in humans at the recommended clinical dose of darunavir co-administered with ritonavir.

Cobicistat: Cobicistat was administered orally to pregnant rats at doses up to 125 mg/kg/day on GD 6–17. Increases in post-implantation loss and decreased fetal weights were observed at a maternal toxic dose of 125 mg/kg/day. No malformations were noted at doses up to 125 mg/kg/day. Systemic exposures (AUC) at 50 mg/kg/day in pregnant females were 1.6 times higher than human exposures at the recommended daily dose of cobicistat.

In pregnant rabbits, cobicistat was administered orally at doses up to 100 mg/kg/day during GD 7–20. No maternal or embryo/fetal effects were noted at the highest dose of 100 mg/kg/day. Systemic exposures (AUC) at 100 mg/kg/day were 3.8 times higher than human exposures at the recommended daily dose of cobicistat.

In a pre/postnatal developmental study in rats, cobicistat was administered orally at doses up to 75 mg/kg from GD 6 to postnatal day 20, 21, or 22. At doses of 75 mg/kg/day, neither maternal nor developmental toxicity was noted. Systemic exposures (AUC) at this dose were 1.2 times the human exposures at the recommended daily dose of cobicistat.

8.2 Lactation

Risk Summary

There are no data on the presence of darunavir or cobicistat in human milk, the effects on the breastfed infant, or the effects on milk production. Darunavir and cobicistat are present in the milk of lactating rats (see Data) . Potential risks of breastfeeding include: (1) HIV-1 transmission (in infants without HIV-1), (2) developing viral resistance (in infants with HIV-1), and (3) serious adverse reactions in breastfed infant similar to those seen in adults.

Data

Animal Data

Darunavir: Studies in rats (with darunavir alone or with ritonavir) have demonstrated that darunavir is excreted in milk. In the rat pre- and postnatal development study, a reduction in pup body weight gain was observed due to exposure of pups to drug substances via milk. The maximal maternal plasma exposures achieved with darunavir (up to 1000 mg/kg with ritonavir) were approximately 50% of those obtained in humans at the recommended clinical dose of darunavir with ritonavir.

Cobicistat: During the pre/postnatal developmental toxicology study at doses up to 75 mg/kg/day, mean cobicistat milk to plasma ratio of up to 1.9 was measured 2 hours after administration to rats on lactation day 10.

8.3 Females and Males of Reproductive Potential

Contraception

Additional or alternative (non-hormonal) forms of contraception should be considered when estrogen-containing contraceptives are co-administered with PREZCOBIX. For co-administration with drospirenone, clinical monitoring is recommended due to the potential for hyperkalemia. No data are available to make recommendations on co-administration with other hormonal contraceptives [see Drug Interactions (7.3)].

8.4 Pediatric Use

The safety and effectiveness of PREZCOBIX for the treatment of HIV-1 in pediatric patients weighing at least 25 kg was established through a trial with components of PREZCOBIX. Use of PREZCOBIX in this group is supported by evidence from adequate and well-controlled studies in adults with additional pharmacokinetic, safety, and virologic data from a study of components of PREZCOBIX (Trial GS-US-216-0128) in pediatric participants with HIV-1 aged 6 to less than 18 years [see Adverse Reactions (6.1), Clinical Pharmacology (12.3), and Clinical Studies (14.2)] .

The safety and effectiveness of PREZCOBIX have not been established in pediatric patients weighing less than 25 kg. Darunavir, a component of PREZCOBIX is not recommended in pediatric patients below 3 years of age because of toxicity and mortality observed in juvenile rats dosed with darunavir.

Juvenile Animal Toxicity Data

Darunavir: In a juvenile toxicity study where rats were directly dosed with darunavir (up to 1000 mg/kg), deaths occurred from post-natal day 5 at plasma exposure levels ranging from 0.1 to 1.0 of the human exposure levels. In a 4-week rat toxicology study, when dosing was initiated on post-natal day 23 (the human equivalent of 2 to 3 years of age), no deaths were observed with a plasma exposure (in combination with ritonavir) 2 times the human plasma exposure levels.

8.5 Geriatric Use

Clinical trials of PREZCOBIX did not include sufficient numbers of patients aged 65 and over to determine whether they respond differently from younger patients. In general, caution should be exercised in the administration and monitoring of PREZCOBIX in elderly patients, reflecting the greater frequency of decreased hepatic function, and of concomitant disease or other drug therapy [see Clinical Pharmacology (12.3)] .

8.6 Hepatic Impairment

No clinical trials were conducted with darunavir co-administered with cobicistat in hepatically impaired patients and the effect of hepatic impairment on darunavir exposure when co-administered with cobicistat has not been evaluated. Based on the recommendations for darunavir co-administered with ritonavir, a dose adjustment for patients with mild or moderate hepatic impairment is not necessary. No pharmacokinetic or safety data are available regarding the use of darunavir in patients with severe hepatic impairment. Therefore, PREZCOBIX is not recommended for use in patients with severe hepatic impairment [see Clinical Pharmacology (12.3)] .

8.7 Renal Impairment

A renal impairment trial was not conducted for darunavir co-administered with cobicistat [see Clinical Pharmacology (12.3)] . Cobicistat has been shown to decrease estimated creatinine clearance without affecting actual renal glomerular function. Dosing recommendations are not available for drugs that require dosage adjustment for renal impairment when used in combination with PREZCOBIX [see Warnings and Precautions (5.3)and Clinical Pharmacology (12.2)] .

10 OVERDOSAGE

Human experience of acute overdose with PREZCOBIX is limited. No specific antidote is available for overdose with PREZCOBIX. Treatment of overdose with PREZCOBIX consists of general supportive measures including monitoring of vital signs and observation of the clinical status of the patient. Since both darunavir and cobicistat are highly protein bound, dialysis is unlikely to be beneficial in significant removal of the active substance.

11 DESCRIPTION

PREZCOBIX® is a fixed-dose combination tablet containing darunavir and cobicistat. Darunavir is an inhibitor of the human immunodeficiency virus (HIV-1) protease. Cobicistat is a mechanism-based inhibitor of cytochrome P450 (CYP) enzymes of the CYP3A family.

PREZCOBIX® 800 mg darunavir/150 mg cobicistat tablets are for oral administration. Each tablet contains darunavir ethanolate equivalent to 800 mg of darunavir and 150 mg of cobicistat. The tablets include the following inactive ingredients: colloidal silicon dioxide, crospovidone, hypromellose, magnesium stearate, and silicified microcrystalline cellulose. The tablets are film-coated with a coating material containing iron oxide black, iron oxide red, polyethylene glycol, polyvinyl alcohol (partially hydrolyzed), talc, and titanium dioxide.

PREZCOBIX® 675 mg darunavir/150 mg cobicistat tablets are for oral administration. Each tablet contains darunavir ethanolate equivalent to 675 mg of darunavir and 150 mg of cobicistat. The tablets include the following inactive ingredients: colloidal silicon dioxide, croscarmellose sodium, magnesium stearate, and microcrystalline cellulose. The tablets are film-coated with a coating material containing iron oxide black, iron oxide yellow, polyethylene glycol, polyvinyl alcohol (partially hydrolyzed), talc, and titanium dioxide.

Darunavir: Darunavir, in the form of darunavir ethanolate, has the following chemical name: [(1 S,2 R)-3-[[(4-aminophenyl)sulfonyl](2-methylpropyl)amino]-2-hydroxy-1-(phenylmethyl)propyl]-carbamic acid (3 R,3a S,6a R)-hexahydrofuro[2,3- b]furan-3-yl ester monoethanolate. Its molecular formula is C27H37N3O7S ∙ C2H5OH and its molecular weight is 593.73. Darunavir ethanolate has the following structural formula:

Cobicistat: Cobicistat is adsorbed onto silicon dioxide. The chemical name for cobicistat is 1,3-thiazol-5-ylmethyl[(2 R, 5 R)-5-{[(2 S)2-[(methyl{[2-(propan-2-yl)-1,3-thiazol-4-yl]methyl}carbamoyl)amino]-4-(morpholin-4yl)butanoyl]amino}-1,6-diphenylhexan-2-yl] carbamate. It has a molecular formula of C40 H53 N7 O5 S2 and a molecular weight of 776.0. It has the following structural formula:

12 CLINICAL PHARMACOLOGY

12.1 Mechanism of Action

PREZCOBIX is a fixed-dose combination of an HIV-1 antiviral drug, darunavir and a CYP3A inhibitor, cobicistat [see Microbiology (12.4)].

12.2 Pharmacodynamics

Cardiac Electrophysiology

Separate thorough QT trials have been conducted for darunavir co-administered with ritonavir and for cobicistat. The effect of darunavir co-administered with cobicistat on the QT interval has not been evaluated.

Darunavir: In a thorough QT/QTc study in 40 healthy participants, darunavir doses (co-administered with 100 mg ritonavir) of approximately 2 times the recommended darunavir dose did not affect the QT/QTc interval.

Cobicistat: The effect of a single dose of cobicistat 250 mg and 400 mg (approximately 1.7 and 2.7 times the recommended dose) on QTc interval was evaluated in a randomized, placebo- and active-controlled (moxifloxacin 400 mg) four-period crossover thorough QT trial in 48 healthy participants. In this trial, no significant QTc prolongation effect of cobicistat was detected. The dose of 400 mg cobicistat is expected to provide information on a high exposure clinical scenario. Prolongation of the PR interval was noted in participants receiving cobicistat in the same trial. The maximum mean (95% upper confidence bound) difference in PR from placebo after baseline-correction was 9.5 (12.1) msec for 250 mg and 20.2 (22.8) msec for 400 mg of cobicistat .

Effects on Serum Creatinine

Cobicistat: The effect of cobicistat on serum creatinine was investigated in a trial in participants with normal renal function (eGFR ≥80 mL/min, N=12) and mild-to-moderate renal impairment (eGFR 50–79 mL/min, N=18). A statistically significant decrease in the estimated glomerular filtration rate, calculated by Cockcroft-Gault method (eGFRCG) from baseline, was observed after 7 days of treatment with cobicistat 150 mg among participants with normal renal function (-9.9 ± 13.1 mL/min) and mild-to-moderate renal impairment (-11.9 ± 7.0 mL/min). No statistically significant changes in eGFRCG were observed compared to baseline for participants with normal renal function or mild-to-moderate renal impairment 7 days after cobicistat was discontinued. The actual glomerular filtration rate, as determined by the clearance of probe drug iohexol, was not altered from baseline following treatment of cobicistat among participants with normal renal function and mild-to-moderate renal impairment, indicating that cobicistat inhibits tubular secretion of creatinine, reflected as a reduction in eGFRCG, without affecting the actual glomerular filtration rate.

12.3 Pharmacokinetics

The pharmacokinetics of darunavir co-administered with cobicistat (150 mg) have been evaluated in healthy adults and in adults with HIV-1.

Darunavir is primarily metabolized by CYP3A. Cobicistat inhibits CYP3A, thereby increasing the plasma concentrations of darunavir.

Under fed (535 total kcal, 171 kcal from fat, 268 kcal from carbohydrates, 96 kcal from protein) and fasted conditions in healthy participants, the 90% confidence intervals when comparing darunavir exposure between PREZCOBIX (800 mg/150 mg) and darunavir 800 mg co-administered with cobicistat 150 mg as single entities were within 80–125%. No clinically significant difference was observed between PREZCOBIX (675 mg/150 mg) and darunavir 675 mg co-administered with cobicistat 150 mg as single entities under fed conditions.

Darunavir exposure when comparing darunavir co-administered with cobicistat (as single entities) to darunavir co-administered with ritonavir was evaluated in a relative bioavailability trial [see cobicistat full prescribing information].Table 3 displays the pharmacokinetic estimates of darunavir after oral administration of darunavir 800 mg co-administered with ritonavir 100 mg once daily (based on sparse sampling in 335 participants in Trial TMC114-C211 and 280 participants in Trial TMC114-C229) and darunavir 800 mg co-administered with cobicistat 150 mg once daily administered as single entities (based on sparse sampling in 298 participants in Trial GS-US-216-0130) to HIV-1 participants.

Table 3: Pharmacokinetic Estimates of Darunavir as Darunavir 800 mg Co-administered with Ritonavir 100 mg Once Daily (Trial TMC114-C211, 48 Week Analysis and Trial TMC114-C229, 48 Week Analysis) and Darunavir 800 mg Co-administered with Cobicistat 150 mg Once Daily (Trial GS-US-216-0130, 24 Week Analysis)
 | Trial TMC114-C211 (treatment-naïve) Darunavir 800 mg co-administered with ritonavir 100 mg once daily | Trial TMC114-C229 (treatment-experienced) Darunavir 800 mg co-administered with ritonavir 100 mg once daily | Trial GS-US-216-0130 (treatment-naïve and experienced) Darunavir 800 mg co-administered with cobicistat 150 mg once daily
Parameter | N=335 | N=280 | N=298
AUC0–24h(ng∙h/mL)
Mean ± SD | 93026 ± 27050 | 93334 ± 28626 | 100152 ± 32042
Median (Range) | 87854 (45000–219240) | 87788 (45456–236920) | 96900 (34500–224000)
C0h(ng/mL)
Mean ± SD | 2282 ± 1168 | 2160 ± 1201 | 2043 ± 1257
Median (Range) | 2041 (368–7242) | 1896 (184–7881) | 1875 (70–6890)
AUC0–24h=area under the concentration-time curve over a 24-hour dosing interval at steady state; C0h=plasma concentration at the end of a 24-hour dosing interval at steady state; N=number of participants; SD=standard deviation

Absorption and Bioavailability

In healthy participants, under fed conditions, when single doses of the darunavir and cobicistat fixed-dose combination tablet were administered, the maximum plasma concentration was achieved within approximately 4 to 4.5 hours for darunavir and approximately 4 to 5 hours for cobicistat.

Effects of Food on Oral Absorption

When compared to fasted conditions, administration of PREZCOBIX to healthy adult participants with a high-fat meal (965 total kcal: 129 kcal from protein, 236 kcal from carbohydrates and 600 kcal from fat) resulted in a 70% increase in AUC(0–inf)and a 127% increase in Cmaxfor darunavir. Cobicistat exposures were not affected by food. PREZCOBIX should be taken with food.

Distribution

Darunavir: Darunavir is approximately 95% bound to plasma proteins. Darunavir binds primarily to plasma alpha 1-acid glycoprotein (AAG).

Cobicistat: Cobicistat is 97–98% bound to human plasma proteins and the mean blood–to-plasma ratio was approximately 0.5.

Metabolism

Darunavir: In vitro experiments with human liver microsomes (HLMs) indicate that darunavir primarily undergoes oxidative metabolism. Darunavir is extensively metabolized by CYP enzymes, primarily by CYP3A. A mass balance trial in healthy participants showed that after single dose administration of 400 mg^14C-darunavir co-administered with 100 mg ritonavir, the majority of the radioactivity in the plasma was due to darunavir. At least 3 oxidative metabolites of darunavir have been identified in humans; all showed activity that was at least 90% less than the activity of darunavir against wild-type HIV-1.

Cobicistat: Cobicistat is metabolized by CYP3A and to a minor extent by CYP2D6 enzymes and does not undergo glucuronidation.

Elimination

Darunavir: A mass balance trial in healthy participants showed that after single dose administration of 400 mg^14C-darunavir co-administered with 100 mg ritonavir, approximately 79.5% and 13.9% of the administered dose of^14C-darunavir was recovered in the feces and urine, respectively. Unchanged darunavir accounted for approximately 41.2% and 7.7% of the administered dose in feces and urine, respectively.

When single doses of the darunavir and cobicistat fixed-dose combination tablet were administered, the terminal elimination half-life of darunavir was approximately 7 hours under fed conditions.

Cobicistat: When single doses of the darunavir and cobicistat fixed-dose combination tablet were administered, the terminal elimination half-life of cobicistat was approximately 4 hours under fed conditions. With single dose administration of^14C-cobicistat after multiple dosing of cobicistat for six days, the mean percent of the administered dose excreted in feces and urine was 86.2% and 8.2%, respectively.

Specific Populations

Hepatic Impairment

Darunavir: Darunavir is primarily metabolized by the liver. The steady-state pharmacokinetic parameters of darunavir were similar after multiple dose co-administration of darunavir 600 mg co-administered with ritonavir 100 mg twice daily to participants with normal hepatic function (n=16), mild hepatic impairment (Child-Pugh Class A, n=8), and moderate hepatic impairment (Child-Pugh Class B, n=8). The effect of severe hepatic impairment on the pharmacokinetics of darunavir has not been evaluated [see Use in Specific Populations (8.6)].

Cobicistat: Cobicistat is primarily metabolized by the liver. A trial evaluating the pharmacokinetics of cobicistat was performed in participants with moderate hepatic impairment. No clinically relevant differences in cobicistat pharmacokinetics were observed between participants with moderate hepatic impairment (Child-Pugh Class B) and healthy participants. The effect of severe hepatic impairment on the pharmacokinetics of cobicistat has not been evaluated [see Use in Specific Populations (8.6)].

Hepatitis B or Hepatitis C Virus Co-Infection

Darunavir: In participants with HIV-1 taking darunavir co-administered with ritonavir, the 48 week analysis of the data from clinical studies in participants with HIV-1 indicated that hepatitis B and/or hepatitis C virus co-infection status had no apparent effect on the exposure of darunavir.

The effect of hepatitis B and/or C virus infection on the pharmacokinetics of PREZCOBIX have not been evaluated.

Renal Impairment

Darunavir: Population pharmacokinetic analysis showed that the pharmacokinetics of darunavir were not significantly affected in participants with HIV-1 with moderate renal impairment taking darunavir co-administered with ritonavir (creatinine clearance between 30–60 mL/min, n=20). There are no pharmacokinetic data available in participants with HIV-1 with severe renal impairment or end stage renal disease taking darunavir co-adminstered with either ritonavir or cobicistat [see Use in Specific Populations (8.7)].

Cobicistat: A trial of the pharmacokinetics of cobicistat was performed in non-HIV participants with severe renal impairment (estimated creatinine clearance below 30 mL/min). No clinically relevant differences in cobicistat pharmacokinetics were observed between participants with severe renal impairment and healthy participants [see Use in Special Populations (8.7)].

Gender

Darunavir: In participants with HIV-1 taking darunavir co-administered with ritonavir, population pharmacokinetic analysis showed higher mean darunavir exposure in females compared to males. This difference is not clinically relevant.

Cobicistat: No clinically relevant pharmacokinetic differences have been observed between men and women for cobicistat.

Race

Darunavir: Population pharmacokinetic analysis of darunavir in participants with HIV-1 taking darunavir co-administered with ritonavir indicated that race had no apparent effect on the exposure to darunavir.

Cobicistat: Population pharmacokinetic analysis of cobicistat in participants with HIV-1 indicated that race had no clinically relevant effect on the exposure of cobicistat.

Geriatric Patients

Darunavir: In participants with HIV-1 taking darunavir co-administered with ritonavir, population pharmacokinetic analysis showed no considerable differences in darunavir pharmacokinetics for ages 18 to 75 years compared to ages greater than or equal to 65 years (n=12) [see Use in Specific Populations (8.5)] .

Cobicistat: Insufficient data are available to determine whether potential differences exist in the pharmacokinetics of cobicistat in geriatric (65 years of age and older) participants compared to younger participants.

Pediatrics Weighing at Least 25 kg

Available pharmacokinetic data for the different components of PREZCOBIX indicate that there were no clinically relevant differences in darunavir exposure between adults and adolescents or children weighing at least 25 kg (see Table 4). Cobicistat exposures were similar between adults and adolescents but higher in children aged 6 to less than 12 years, weighing at least 25 kg. The difference observed in children for cobicistat is not considered clinically relevant.

Table 4: Pharmacokinetic Estimates Comparison of Darunavir AUC0–24hand C0hin Pediatric and Adult Studies
Parameter | GS-US-216-0128 in Participants Aged ≥ 6 to < 12 Years and Weighing ≥ 25 to < 40 kg DRV 675 mg/COBI 150 mg N=8 | GS-US-216-0128 in Participants Aged ≥ 12 to < 18 Years and Weighing ≥ 40 kg DRV 800 mg/COBI 150 mg N=8 | TMC114FD2HTX3001 in Adult Participants DRV 800 mg/COBI 150 mg/FTC 200 mg/TAF 10 mg N=356
AUC0–24h(ng ∙ h/mL) [Mean ± standard deviation] | 92,052 ±17,254 | 69,474 ±10,359 | 87,909 ±20,232
C0h(ng/mL) | 1,345 ±569 | 938 ±445 | 1,899 ±759
AUC0–24h=area under the concentration-time curve over a 24-hour dosing interval at steady state; C0h=plasma concentration at the end of a 24-hour dosing interval at steady state; COBI=cobicistat; DRV=darunavir; FTC=emtricitabine; N=number of participants; TAF=tenofovir alafenamide

Pregnancy and Postpartum

The exposure to total and unbound darunavir boosted with cobicistat after intake of PREZCOBIX as part of an antiretroviral regimen was substantially lower during the second and third trimesters of pregnancy compared with 6–12 weeks postpartum (see Table 5 and Figure 1).

Table 5: Pharmacokinetic Results of Total Darunavir after Administration of PREZCOBIX Once Daily as Part of an Antiretroviral Regimen, During the 2nd Trimester of Pregnancy, the 3rd Trimester of Pregnancy, and Postpartum
Parameter | 2ndTrimester of pregnancy N=7 | 3rdTrimester of pregnancy N=6 | Postpartum (6–12 weeks) N=6
Cmax(ng/mL) [Mean ± standard deviation] | 4340 ± 1616 | 4910 ± 970 | 7918 ± 2199
AUC0–24h(ng∙h/mL) | 47293 ± 19058 | 47991 ± 9879 | 99613 ± 34862
Cmin(ng/mL) | 168 ± 149 | 184 ± 99 | 1538 ± 1344
Cmax=maximum plasma concentration at steady state; AUC0–24h=area under the concentration-time curve over a 24-hour dosing interval at steady state; Cmin=minimum plasma concentration at steady state

Figure 1: Pharmacokinetic Results (Within-Subject Comparison) of Total and Unbound Darunavir and Total Cobicistat after Administration of PREZCOBIX at 800/150 mg Once Daily as Part of an Antiretroviral Regimen, During the 2ndand 3rdTrimester of Pregnancy Compared to Postpartum

Legend: 90% CI: 90% confidence interval; GMR: geometric mean ratio (i.e. second or third trimester / postpartum). Solid vertical line: ratio of 1.0; dotted vertical lines: reference lines of 0.8 and 1.25.

Drug Interactions

Darunavir is metabolized by CYP3A. Cobicistat is metabolized by CYP3A and, to a minor extent, by CYP2D6. Darunavir co-administered with cobicistat is an inhibitor of CYP3A and CYP2D6. Cobicistat inhibits the following transporters: P-gp, BCRP, MATE1, OATP1B1, and OATP1B3. Based on in vitro data, cobicistat is not expected to induce CYP1A2 or CYP2B6 and based on in vivo data, cobicistat is not expected to induce MDR1 or, in general, CYP3A to a clinically significant extent. The induction effect of cobicistat on CYP2C9, CYP2C19, or UGT1A1 is unknown, but is expected to be low based on CYP3A in vitro induction data [see Drug Interactions (7)] .

A drug-drug interaction study between darunavir/cobicistat and dabigatran etexilate was conducted in healthy participants. The effects of darunavir on co-administration with dabigatran etexilate are summarized in Table 6.

Table 6: Drug Interactions: Pharmacokinetic Parameters for Co-Administered Drugs in the Presence of darunavir/cobicistat
Co-administered drug | Dose/Schedule |  | N | PK | LS Mean ratio (90% CI) of co-administered drug pharmacokinetic parameters with/without darunavir no effect =1.00
Co-administered drug | Co-administered drug | Darunavir/ cobicistat | N | PK | Cmax | AUC | Cmin
Dabigatran etexilate | 150 mg | 800/150 mg single dose | 14 | ↑ | 2.64 (2.29–3.05) | 2.64 (2.32–3.00) | -
 |  | 800/150 mg q.d. [800/150 mg q.d. for 14 days before co-administered with dabigatran etexilate.] | 14 | ↑ | 1.99 (1.72–2.30) | 1.88 (1.65–2.13) | -
N = number of participants with data
q.d. = once daily

12.4 Microbiology

Mechanism of Action

Darunavir: Darunavir is an inhibitor of the HIV-1 protease. It selectively inhibits the cleavage of HIV-1 encoded Gag-Pol polyproteins in infected cells, thereby preventing the formation of mature virus particles.

Cobicistat: Cobicistat is a selective, mechanism-based inhibitor of cytochromes P450 of the CYP3A subfamily. Inhibition of CYP3A-mediated metabolism by cobicistat enhances the systemic exposure of CYP3A substrates.

Antiviral Activity

Darunavir: Darunavir exhibits activity against laboratory strains and clinical isolates of HIV-1 and laboratory strains of HIV-2 in acutely infected T-cell lines, human peripheral blood mononuclear cells, and human monocytes/macrophages with median EC50 values ranging from 1.2 to 8.5 nM (0.7 to 5.0 ng/mL). Darunavir demonstrates antiviral activity in cell culture against a broad panel of HIV-1 group M (A, B, C, D, E, F, G), and group O primary isolates with EC50 values ranging from less than 0.1 to 4.3 nM. The EC50 value of darunavir increases by a median factor of 5.4 in the presence of human serum. Darunavir did not show antagonism when studied in combination with the HIV protease inhibitors (PIs) amprenavir, atazanavir, indinavir, lopinavir, nelfinavir, ritonavir, saquinavir, or tipranavir, the N(t)RTIs abacavir, didanosine, emtricitabine, lamivudine, stavudine, tenofovir, zalcitabine, or zidovudine, the NNRTIs delavirdine, efavirenz, etravirine, rilpivirine, or nevirapine, and the fusion inhibitor enfuvirtide.

Cobicistat: Cobicistat does not inhibit recombinant HIV-1 protease in a biochemical assay and has no detectable antiviral activity in cell culture against HIV-1. The antiviral activity in cell culture of approved HIV-1 antiretroviral drugs was not antagonized by cobicistat.

Resistance

Cell Culture

Darunavir: HIV-1 isolates with a decreased susceptibility to darunavir have been selected in cell culture and obtained from participants treated with darunavir co-administered with ritonavir. Darunavir-resistant virus derived in cell culture from wild-type HIV-1 had 21- to 88-fold decreased susceptibility to darunavir and developed 2 to 4 of the following amino acid substitutions S37D, R41E/T, K55Q, H69Q, K70E, T74S, V77I, or I85V in the protease. Selection in cell culture of darunavir resistant HIV-1 from nine HIV-1 strains harboring multiple PI resistance-associated substitutions resulted in the overall emergence of 22 mutations in the protease gene, coding for amino acid substitutions L10F, V11I, I13V, I15V, G16E, L23I, V32I, L33F, S37N, M46I, I47V, I50V, F53L, L63P, A71V, G73S, L76V, V82I, I84V, T91A/S, and Q92R, of which L10F, V32I, L33F, S37N, M46I, I47V, I50V, L63P, A71V, and I84V were the most prevalent. These darunavir-resistant viruses had at least eight protease substitutions and exhibited 50- to 641-fold decreases in darunavir susceptibility with final EC50values ranging from 125 nM to 3461 nM.

Clinical Studies

The resistance profile of PREZCOBIX is driven by darunavir. Cobicistat does not select any HIV resistance substitutions, due to its lack of antiviral activity. For the clinical resistance profile of darunavir, refer to the darunavir full prescribing information.

Cross-resistance

Cross-resistance among PIs has been observed. Darunavir has a less than 10-fold decreased susceptibility in cell culture against 90% of 3309 clinical isolates resistant to amprenavir, atazanavir, indinavir, lopinavir, nelfinavir, ritonavir, saquinavir, and/or tipranavir showing that viruses resistant to these PIs remain susceptible to darunavir. A less than 10-fold decreased susceptibility was observed for the other PIs in 26% to 96% of these PI resistant clinical isolates [nelfinavir (26%), ritonavir (34%), lopinavir (46%), indinavir (57%), atazanavir (59%), saquinavir (64%), amprenavir (70%), and tipranavir (96%)].

Cross-resistance between darunavir and nucleoside/nucleotide reverse transcriptase inhibitors, non-nucleoside reverse transcriptase inhibitors, fusion inhibitors, CCR5 co-receptor antagonists, or integrase strand transfer inhibitors is unlikely because the viral targets are different.

Baseline Genotype/Phenotype and Virologic Outcome Analyses

Baseline International AIDS Society (IAS)-defined PI resistance substitutions confer reduced virologic response to darunavir. Please refer to the "Baseline Genotype/Phenotype and Virologic Outcome Analyses" section in the darunavir full prescribing information.

13 NONCLINICAL TOXICOLOGY

13.1 Carcinogenesis, Mutagenesis, Impairment of Fertility

Carcinogenesis and Mutagenesis

Darunavir: Darunavir was evaluated for carcinogenic potential by oral gavage administration to mice and rats up to 104 weeks. Daily doses of 150, 450 and 1000 mg/kg were administered to mice and doses of 50, 150 and 500 mg/kg were administered to rats. A dose-related increase in the incidence of hepatocellular adenomas and carcinomas was observed in males and females of both species and an increase in thyroid follicular cell adenomas was observed in male rats. The observed hepatocellular findings in rodents are considered to be of limited relevance to humans. Repeated administration of darunavir to rats caused hepatic microsomal enzyme induction and increased thyroid hormone elimination, which predispose rats but not humans, to thyroid neoplasms. At the highest tested doses, the systemic exposures to darunavir (based on AUC) were between 0.4- and 0.7-fold (mice) and 0.7- and 1-fold (rats) of exposures observed in humans at the recommended therapeutic doses (darunavir 600 mg co-administered with ritonavir 100 mg twice daily or darunavir 800 mg co-administered with ritonavir 100 mg once daily).

Darunavir was not mutagenic or genotoxic in a battery of in vitro and in vivo assays including bacterial reverse mutation (Ames), chromosomal aberration in human lymphocytes, and in vivo micronucleus test in mice.

Cobicistat: In a long-term carcinogenicity study in mice, no drug-related increases in tumor incidence were observed at doses up to 50 and 100 mg/kg/day in males and females, respectively. Cobicistat exposures at these doses were approximately 7 (male) and 16 (females) times, respectively, the human systemic exposure at the therapeutic daily dose. In a long-term carcinogenicity study of cobicistat in rats, an increased incidence of follicular cell adenomas and/or carcinomas in the thyroid gland was observed at doses of 25 and 50 mg/kg/day in males, and at 30 mg/kg/day in females. The follicular cell findings are considered to be rat-specific, secondary to hepatic microsomal enzyme induction and thyroid hormone imbalance, and are not relevant for humans. At the highest doses tested in the rat carcinogenicity study, systemic exposures were approximately 2 times the human systemic exposure at the therapeutic daily dose.

Cobicistat was not genotoxic in the reverse mutation bacterial test (Ames test), mouse lymphoma or rat micronucleus assays.

Impairment of Fertility

Darunavir: No effects on fertility or early embryonic development were observed with darunavir in rats.

Cobicistat: Cobicistat did not affect fertility in male or female rats at daily exposures (AUC) approximately 4-fold higher than human exposures at the recommended 150 mg daily dose.

Fertility was normal in the offspring of rats exposed daily from before birth (in utero) through sexual maturity at daily exposures (AUC) of approximately 1.2-fold higher than human exposures at the recommended 150 mg daily dose.

14 CLINICAL STUDIES

14.1 Clinical Trial Results in Adults with HIV-1

The efficacy of PREZCOBIX in adults with HIV-1 is based on efficacy demonstrated in clinical trials of darunavir co-administered with ritonavir [see darunavir full prescribing information].

14.2 Clinical Trial Results in Pediatrics with HIV-1

Trial GS-US-216-0128 was a Phase 2/3 multicenter, open-label trial to evaluate the pharmacokinetics, safety, and efficacy of darunavir co-administered with cobicistat in adolescents aged 12 years and older (Cohort 1) and children aged 6 to less than 12 years old (Cohort 2) with HIV-1 who were virologically suppressed and had a baseline estimated creatinine clearance ≥90 mL/min/1.73 m^2. Participants were on a stable antiretroviral regimen including at least 2 NRTIs (for at least 3 months).

Cohort 1: The median age of participants was 14 years (range 12–16 years), median weight was 60 kg (range 45–78 kg), and 43% were male. At baseline, all had plasma HIV-1 RNA <50 copies/mL. At Week 48, 86% (6/7) of participants remained suppressed (HIV-1 RNA <50 copies/mL), and 1 had missing data. From a median baseline CD4+ cell count and CD4+% of 1,117 cells/mm^3 (range 658 to 2,416 cells/mm^3) and 45% (range 28% to 56%), respectively, the median change from baseline in CD4+ cell count and CD4+% at Week 48 was -342 cells/mm^3 (range -1,389 to 219 cells/mm^3) and -6% (range -12% to 5%), respectively. All 6 participants with available data had CD4+ cell counts above 800 cells/mm^3 at Week 48.

Cohort 2: The median age of participants was 10 years (range 7–11 years), median weight was 31.7 kg (range 29.1–45.4 kg), and 75% were female. At baseline, all had plasma HIV-1 RNA <50 copies/mL. At Week 48, all participants remained suppressed (HIV-1 RNA <50 copies/mL). From a median baseline CD4+ cell count and CD4+% of 998 cells/mm^3 (range 439 to 1113 cells/mm^3) and 40% (range 29.1% to 48.5%), respectively, the median change from baseline in CD4+ cell count and CD4+% at Week 48 was -20 cells/mm^3 (range -318 to 245) and 0.75% (-11.40 to 3.20), respectively.

16 HOW SUPPLIED/STORAGE AND HANDLING

PREZCOBIX® (darunavir and cobicistat) tablets, 800/150 mg, are supplied as pink, oval-shaped, film-coated tablets debossed with "800" on one side and "TG" on the other side. Bottle of 30 tablets (NDC 59676-575-30).

PREZCOBIX®(darunavir and cobicistat) tablets, 675/150 mg, are supplied as green to dark green, oval-shaped, scored film-coated tablet debossed with “675” on one side and “TG” on the other side. Bottle of 30 tablets (NDC 59676-578-30).

STORAGE AND HANDLING

Storage: Store at 20 °C–25 °C (between 68 °F–77 °F); with excursions permitted to 15 °C–30 °C (59 °F–86 °F) [see USP Controlled Room Temperature].

Keep PREZCOBIX and all medicines out of reach of children.

17 PATIENT COUNSELING INFORMATION

Advise the patient to read the FDA-approved patient labeling (Patient Information).

Instructions for Use

Advise patients to take PREZCOBIX with food every day on a regular dosing schedule, as missed doses can result in development of resistance. Inform patients not to alter the dose of PREZCOBIX or discontinue therapy with PREZCOBIX without consulting their physician [see Dosage and Administration (2.2)].

Hepatotoxicity

Inform patients that drug-induced hepatitis (e.g., acute hepatitis, cytolytic hepatitis) and liver injury, including some fatalities, could potentially occur with PREZCOBIX. Advise patients to contact their healthcare provider immediately if signs and symptoms of liver problems develop [see Warnings and Precautions (5.1)] .

Severe Skin Reactions

Inform patients that skin reactions ranging from mild to severe, including Stevens-Johnson Syndrome, drug rash with eosinophilia and systemic symptoms, and toxic epidermal necrolysis, could potentially occur with PREZCOBIX. Advise patients to contact their healthcare provider immediately if signs or symptoms of severe skin reactions develop, including but not limited to severe rash or rash accompanied with fever, general malaise, fatigue, muscle or joint aches, blisters, oral lesions, and/or conjunctivitis [see Warnings and Precautions (5.2)] .

Renal Impairment

Inform patients that renal impairment, including cases of acute renal failure and Fanconi syndrome, has been reported when cobicistat is used in combination with a tenofovir DF-containing regimen [see Warnings and Precautions (5.4)] .

Pregnancy

Advise patients that PREZCOBIX is not recommended during pregnancy and to alert their healthcare provider if they get pregnant while taking PREZCOBIX [see Use in Specific Populations (8.1)] . Inform patients that there is an antiretroviral pregnancy registry to monitor fetal outcomes of pregnant individuals exposed to PREZCOBIX [see Use in Specific Populations (8.1)].

Lactation

Inform patients that the potential risks of breastfeeding include: (1) HIV-1 transmission (in infants without HIV-1), (2) developing viral resistance (in infants with HIV-1), and (3) serious adverse reactions in a breastfed infant similar to those seen in adults [see Use in Specific Populations (8.2)] .

Drug Interactions

PREZCOBIX may interact with many drugs; therefore, inform patients of the potential serious drug interactions with PREZCOBIX, and that some drugs are contraindicated with PREZCOBIX and other drugs may require dosage adjustment. Advise patients to report to their healthcare provider the use of any other prescription or nonprescription medication or herbal products, including St. John's wort.

Immune Reconstitution Syndrome

Advise patients to inform their healthcare provider immediately of any symptoms of infection, as in some patients with advanced HIV infection (AIDS), signs and symptoms of inflammation from previous infections may occur soon after anti-HIV treatment is started [see Warnings and Precautions (5.10)] .

Fat Redistribution

Inform patients that redistribution or accumulation of body fat may occur in patients receiving antiretroviral therapy, including PREZCOBIX and that the cause and long-term health effects of these conditions are not known at this time [see Warnings and Precautions (5.9)] .

Manufactured for:
Janssen Products, LP, Horsham, PA 19044, USA

For patent information: www.janssenpatents.com

© Johnson & Johnson and its affiliates 2015, 2025

PATIENT INFORMATION
PREZCOBIX® (prez-koe-bix)
(darunavir and cobicistat)
tablets

What is the most important information I should know about PREZCOBIX?
PREZCOBIX may cause serious side effects, including:

- Liver problems. People taking PREZCOBIX may develop liver problems which may be life-threatening and can lead to death. Your healthcare provider should do blood tests before and during your treatment with PREZCOBIX. If you have chronic hepatitis B or C infection or other liver problems, your healthcare provider may check your blood tests more often because you have an increased risk of developing liver problems. Tell your healthcare provider right away if you develop any new or worsening signs or symptoms of liver problems, including:

- tiredness
- dark (tea colored) urine
- yellowing of your skin or whites of your eyes
- pale colored stools (bowel movements)
- nausea

- vomiting
- pain or tenderness on your right side below your ribs
- loss of appetite

- Severe skin reactions or rash. Skin rash is common during treatment with PREZCOBIX but can become severe and require treatment in a hospital. Call your healthcare provider right away if you develop a rash. Stop taking PREZCOBIX and call your healthcare provider right away if you develop a severe rash or a rash with any of the following symptoms:

- fever
- tiredness
- muscle or joint pain

- blisters or skin lesions
- mouth sores or ulcers
- red or inflamed eyes, like "pink eye" (conjunctivitis)

- Kidney problems. PREZCOBIX when taken with certain other medicines can cause new or worsening kidney problems, including kidney failure. Your healthcare provider should check your kidneys before you start and during treatment with PREZCOBIX.

See " What are the possible side effects of PREZCOBIX?" for more information about side effects.

What is PREZCOBIX?
PREZCOBIX is a prescription medicine that is used with other human immunodeficiency virus (HIV-1) medicines to treat HIV-1 in adults and in children who weigh at least 55 pounds (25 kg).
HIV-1 is the virus that causes Acquired Immune Deficiency Syndrome (AIDS).
PREZCOBIX contains the prescription medicines darunavir and cobicistat.
It is not known if PREZCOBIX is safe and effective in children weighing less than 55 pounds (25 kg).

Do not take PREZCOBIX with any medicine that contains:

- alfuzosin
- carbamazepine
- colchicine, if you have liver or kidney problems
- dronedarone
- elbasvir and grazoprevir
- ergot-containing medicines:
  - dihydroergotamine
  - ergotamine tartrate
  - methylergonovine
- ivabradine
- lomitapide
- lovastatin
- lurasidone
- midazolam, when taken by mouth
- naloxegol
- phenobarbital
- phenytoin
- pimozide
- ranolazine
- rifampin
- sildenafil, when used for the treatment of pulmonary arterial hypertension (PAH)
- simvastatin
- St. John's wort (Hypericum perforatum)
- triazolam

Serious problems can happen if you take any of these medicines with PREZCOBIX. This is not a complete list of medicines. Therefore, tell your healthcare provider about all medicines you take.

Before taking PREZCOBIX, tell your healthcare provider about all your medical conditions, including if you:

- have liver problems, including hepatitis B or hepatitis C, or liver disease (cirrhosis)
- have kidney problems
- are allergic to sulfa (sulfonamide)
- have diabetes
- have hemophilia
- are pregnant or plan to become pregnant.
  - It is not known if PREZCOBIX will harm your unborn baby.
  - PREZCOBIX should not be used during pregnancy because the PREZCOBIX levels in your blood may be lower during pregnancy and may not control your HIV-1.
  - Tell your healthcare provider right away if you become pregnant during treatment with PREZCOBIX.
  - Your healthcare provider will prescribe different medicines if you become pregnant during treatment with PREZCOBIX.
  - Hormonal forms of birth control, such as injections, vaginal rings or implants, contraceptive patches, and some birth control pills may not work during treatment with PREZCOBIX. Talk to your healthcare provider about forms of birth control that may be used during treatment with PREZCOBIX.
  - Pregnancy Exposure Registry: There is a pregnancy exposure registry for people who take PREZCOBIX during pregnancy. The purpose of the registry is to collect information about the health of you and your baby. Talk to your healthcare provider about how you can take part in this registry.
- are breastfeeding or plan to breastfeed. It is not known if PREZCOBIX passes into your breast milk.
  - Talk to your healthcare provider about the following risks of breastfeeding during treatment with PREZCOBIX:
    - The HIV-1 virus may pass to your baby if your baby does not have HIV-1.
    - The HIV-1 virus may become harder to treat if your baby has HIV-1.
    - Your baby may get side effects from PREZCOBIX.

Tell your healthcare provider about all the medicines you take, including prescription and over-the-counter medicines, topical creams, vitamins, and herbal supplements. Some medicines interact with PREZCOBIX. Keep a list of your medicines to show your healthcare provider and pharmacist.

- You can ask your healthcare provider or pharmacist for a list of medicines that interact with PREZCOBIX.
- Do not start taking a new medicine without telling your healthcare provider. Your healthcare provider can tell you if it is safe to take PREZCOBIX with other medicines.

How should I take PREZCOBIX?

- Take PREZCOBIX exactly as your healthcare provider tells you to take it.
- Do not change your dose or stop taking PREZCOBIX without talking to your healthcare provider. Stay under a healthcare provider’s care during treatment with PREZCOBIX.
- Take PREZCOBIX 1 time a day with food.
- For children weighing at least 55 pounds (25 kg) who cannot swallow a tablet whole: The scored tablet can be split by hand into 2 pieces. The score line will help you break the tablet. After splitting the tablet, swallow the 2 pieces right away to get the full dose of PREZCOBIX.
- When your PREZCOBIX supply starts to run low, get more from your healthcare provider or pharmacy. This is very important because the amount of virus in your blood may increase if the medicine is stopped for even a short time. The virus may develop resistance to PREZCOBIX and become harder to treat.
- If you take too much PREZCOBIX, call your healthcare provider or go to the nearest hospital emergency room right away.

What are the possible side effects of PREZCOBIX?

- See " What is the most important information I should know about PREZCOBIX?"

PREZCOBIX may cause serious side effects, including:

- Diabetes and high blood sugar (hyperglycemia). New or worsening diabetes and hyperglycemia have happened in people who take protease inhibitors including PREZCOBIX. Some people have had to start taking medicine to treat diabetes or have had to change their diabetes medicine. Tell your healthcare provider if you notice an increase in thirst or if you start urinating more often during treatment with PREZCOBIX.
- Changes in body fat can happen in people who take HIV-1 medications. The changes may include an increased amount of fat in the upper back and neck ("buffalo hump"), breast, and around the middle of your body (trunk). Loss of fat from the legs, arms, and face may also happen. The exact cause and long-term health effects of these conditions are not known.
- Changes in your immune system (Immune Reconstitution Syndrome) can happen when you start taking HIV-1 medicines. Your immune system may get stronger and begin to fight infections that have been hidden in your body for a long time. Tell your healthcare provider right away if you have any symptoms of infection after starting your HIV-1 medicine.
- Increased bleeding for people with hemophilia. Some people with hemophilia have increased bleeding with protease inhibitors including PREZCOBIX.

The most common side effects of darunavir, one of the medicines in PREZCOBIX, include:

- diarrhea
- nausea
- rash

- headache
- stomach-area (abdominal) pain
- vomiting

These are not all of the possible side effects of PREZCOBIX.
Call your doctor for medical advice about side effects. You may report side effects to FDA at 1-800-FDA-1088.

How should I store PREZCOBIX?

- Store PREZCOBIX tablets at room temperature between 68 °F to 77 °F (20 °C to 25 °C).

Keep PREZCOBIX and all medicines out of reach of children.

General information about the safe and effective use of PREZCOBIX.
Medicines are sometimes prescribed for purposes other than those listed in a Patient Information leaflet. Do not use PREZCOBIX for a condition for which it was not prescribed. Do not give PREZCOBIX to other people, even if they have the same symptoms that you have. It may harm them.
You can ask your pharmacist or healthcare provider for information about PREZCOBIX that is written for health professionals.

What are the ingredients in PREZCOBIX?
Active ingredients: darunavir and cobicistat
Inactive ingredients 800 mg/150 mg tablet: colloidal silicon dioxide, crospovidone, hypromellose, magnesium stearate, and silicified microcrystalline cellulose. The tablets are film-coated with a coating material containing iron oxide black, iron oxide red, polyethylene glycol, polyvinyl alcohol (partially hydrolyzed), talc, and titanium dioxide.
Inactive ingredients 675 mg/150 mg tablet: colloidal silicon dioxide, croscarmellose sodium, magnesium stearate, and microcrystalline cellulose. The tablets are film-coated with a coating material containing iron oxide black, iron oxide yellow, polyethylene glycol, polyvinyl alcohol (partially hydrolyzed), talc, and titanium dioxide.
Manufactured for: Janssen Products, LP, Horsham, PA 19044, USA
For patent information: www.janssenpatents.com © Johnson & Johnson and its affiliates 2015, 2025
For more information call 1-800-526-7736.

This Patient Information has been approved by the U.S. Food and Drug Administration.

Revised: 03/2025

PRINCIPAL DISPLAY PANEL - 800 mg/150 mg Tablet Bottle Label

NDC 59676-575-30

PREZCOBIX®
(darunavir and cobicistat)
Tablets

800 mg/150 mg

ALERT: Find out about medicines

that should NOT be taken with PREZCOBIX®

from your healthcare provider.

Rx only

30 Tablets

Johnson

&Johnson

PRINCIPAL DISPLAY PANEL - 675 mg/150 mg Tablet Bottle Carton

NDC 59676-578-30

PREZCOBIX®
(darunavir and
cobicistat)

Tablets

675 mg/150 mg

ALERT: Find out about medicines that
should NOT be taken with PREZCOBIX®
from your healthcare provider.

Rx only
30 Tablets

Johnson
& Johnson